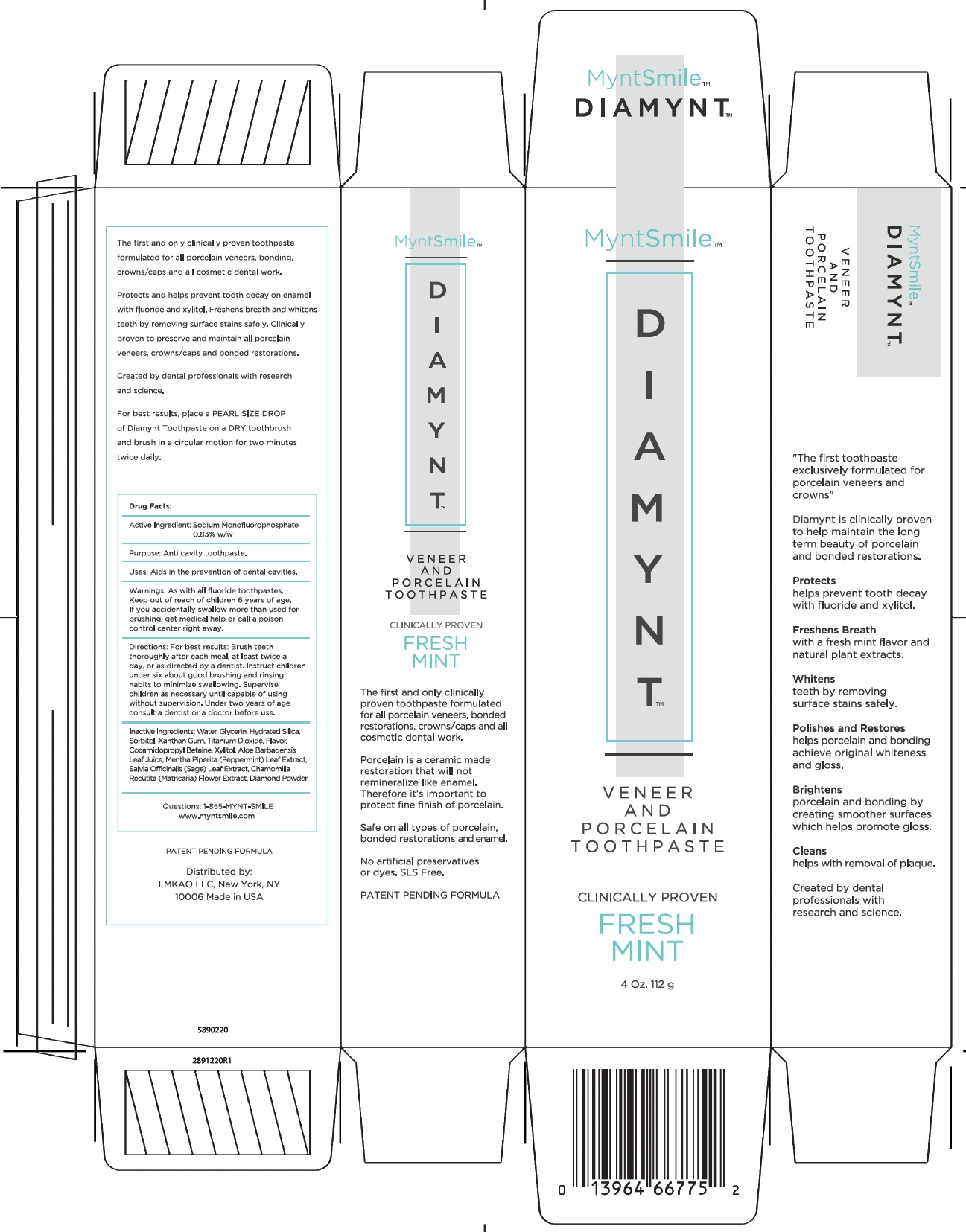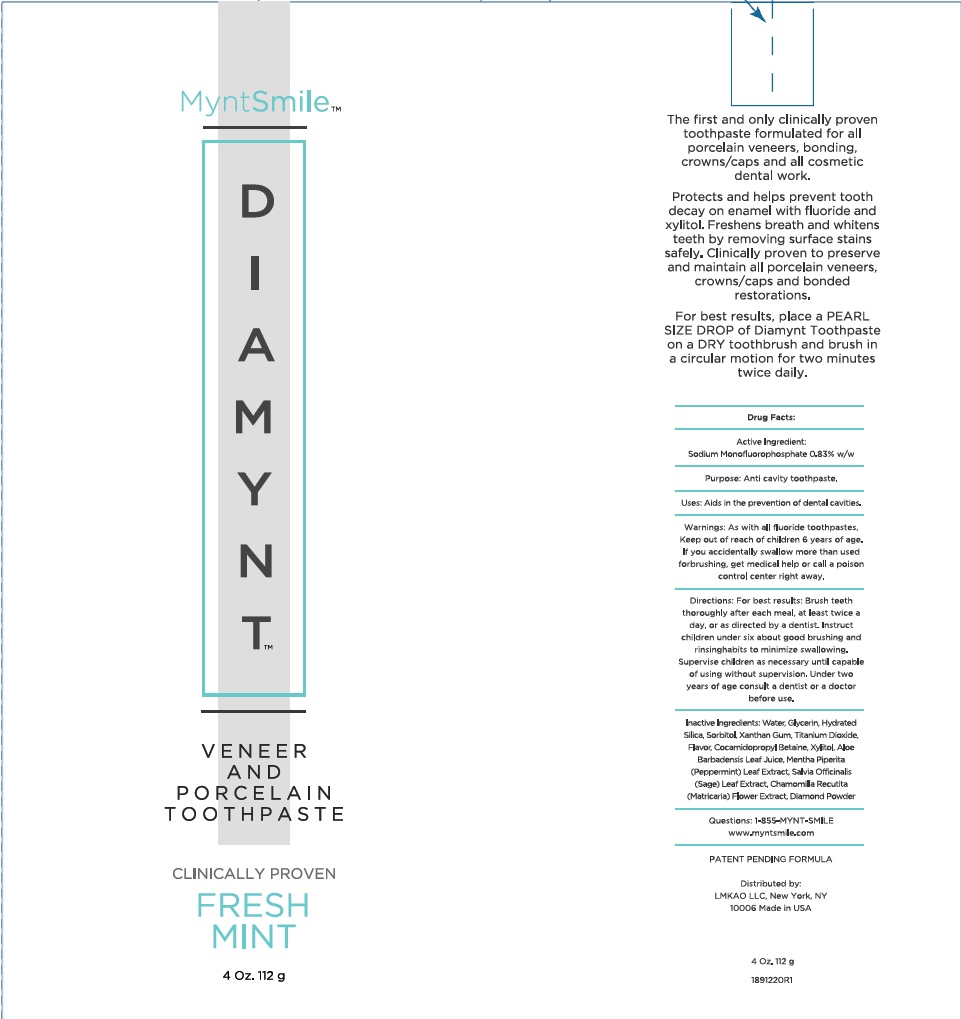 DRUG LABEL: MyntSmile
NDC: 42357-001 | Form: PASTE, DENTIFRICE
Manufacturer: LMKAO LLC
Category: otc | Type: HUMAN OTC DRUG LABEL
Date: 20120310

ACTIVE INGREDIENTS: SODIUM MONOFLUOROPHOSPHATE 0.83 g/100 g
INACTIVE INGREDIENTS: WATER; GLYCERIN; HYDRATED SILICA; GLYCERIN; ALUMINUM OXIDE; HYDRATED SILICA; SORBITOL; XANTHAN GUM; TITANIUM DIOXIDE; COCAMIDOPROPYL BETAINE; XYLITOL; ALOE VERA LEAF; MENTHA PIPERITA; SAGE; CHAMOMILE FLOWER OIL; DIAMOND

MYNTSMILE DIAMYNT

Active Ingredient:

Sodium Monofluorophosphate 0.83% w/w

Purpose:

Anti cavity toothpaste.

Uses:

Aids in the prevention of dental cavities.

Warnings:

As with all fluoride toothpastes, Keep out of reach of children under 6 yrs of age.

If you accidentally swallow more than used for brushing, get medical help or contact a poison control center right away.

Directions

For best results: Brush teeth thoroughly after each meal, at least twice a day, or as directed by a dentist. Instruct children under six about good brushing and rinsing habits to minimize swallowing.

Supervise children as necessary until capable of using without supervision. Under two years of age consult a dentist or a doctor before use.

Inactive ingredients:

Water, Glycerin, Hydrated Silica, Sorbitol, Xanthan Gum, Titanium Dioxide, Flavor, Cocamidopropyl Betaine, Xylitol, Aloe Barbadensis Leaf Juice, Mentha Piperita (Peppermint) Leaf Extract, Salvia Officinalis (Sage) Leaf Extract, Chamomilla Recutita (Matricaria) Flower Extarct, Diamond Powder

Questions: 1-855-MYNT-SMILE

www.myntsmile.com

PATENT PENDING FORMULA

Distributed by:

LMKAO LLC, New York, NY

10006 Made in USA

DIAMYNT TUBE LABEL

DIAMYNT BOX LABEL